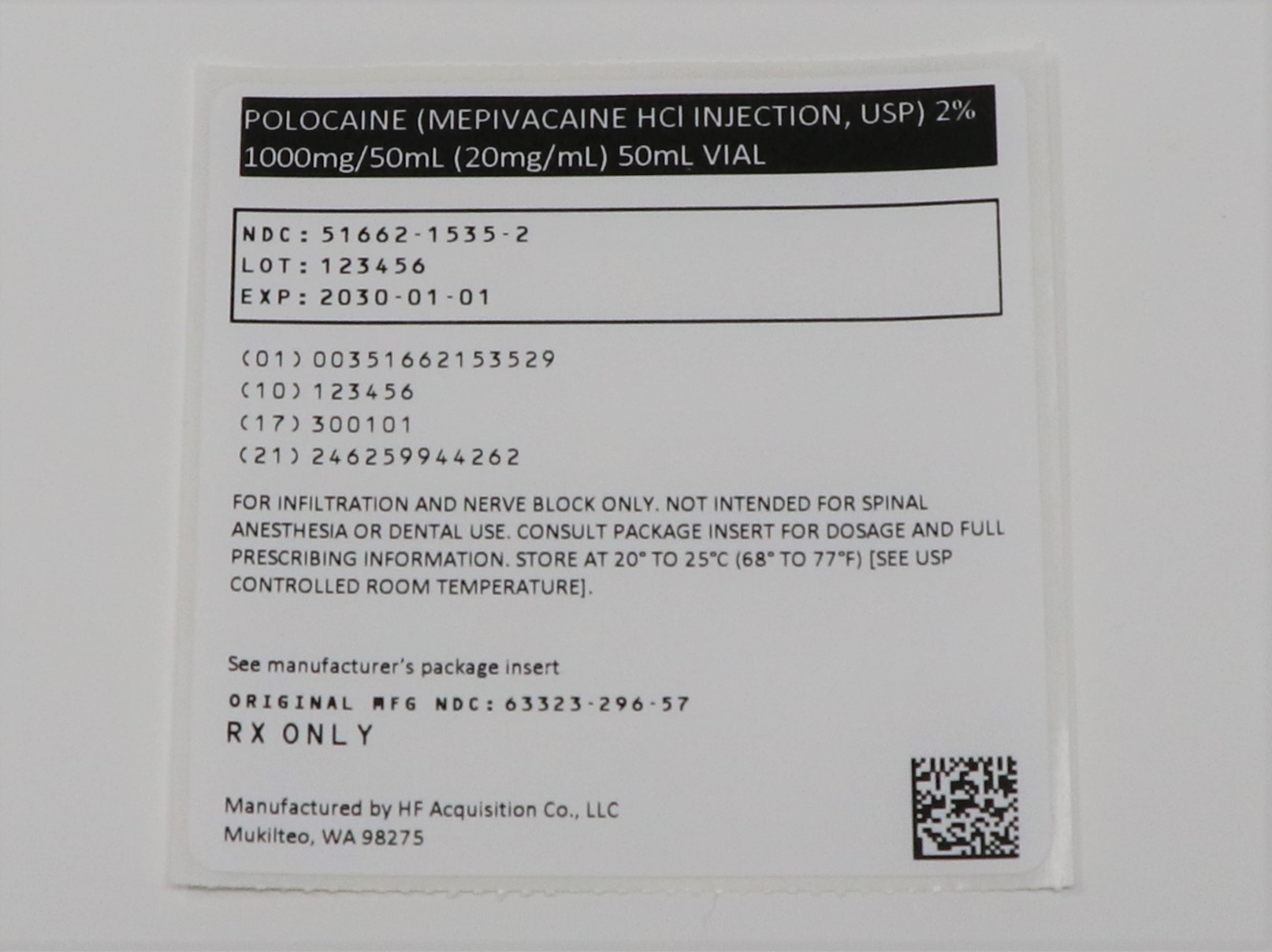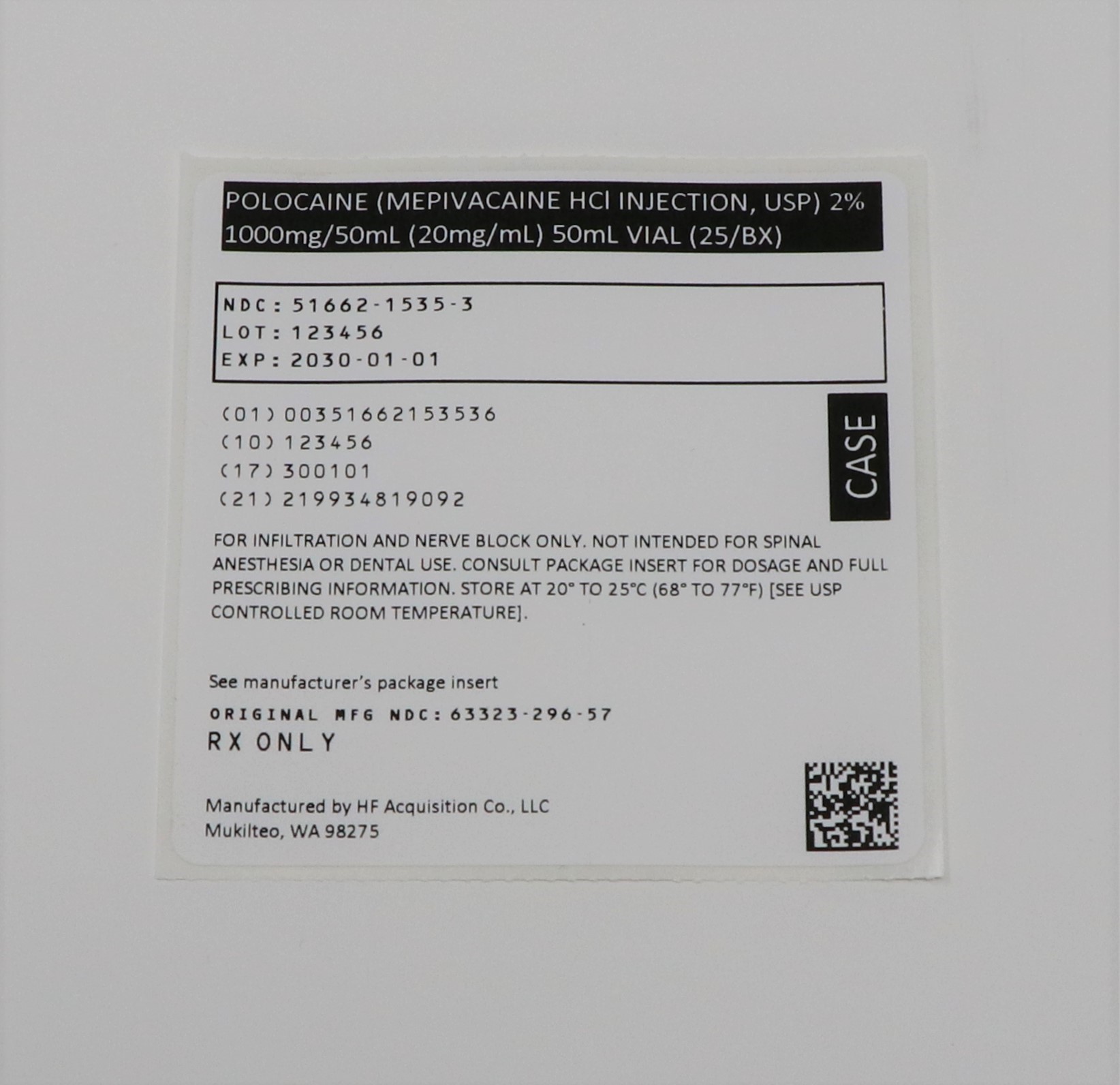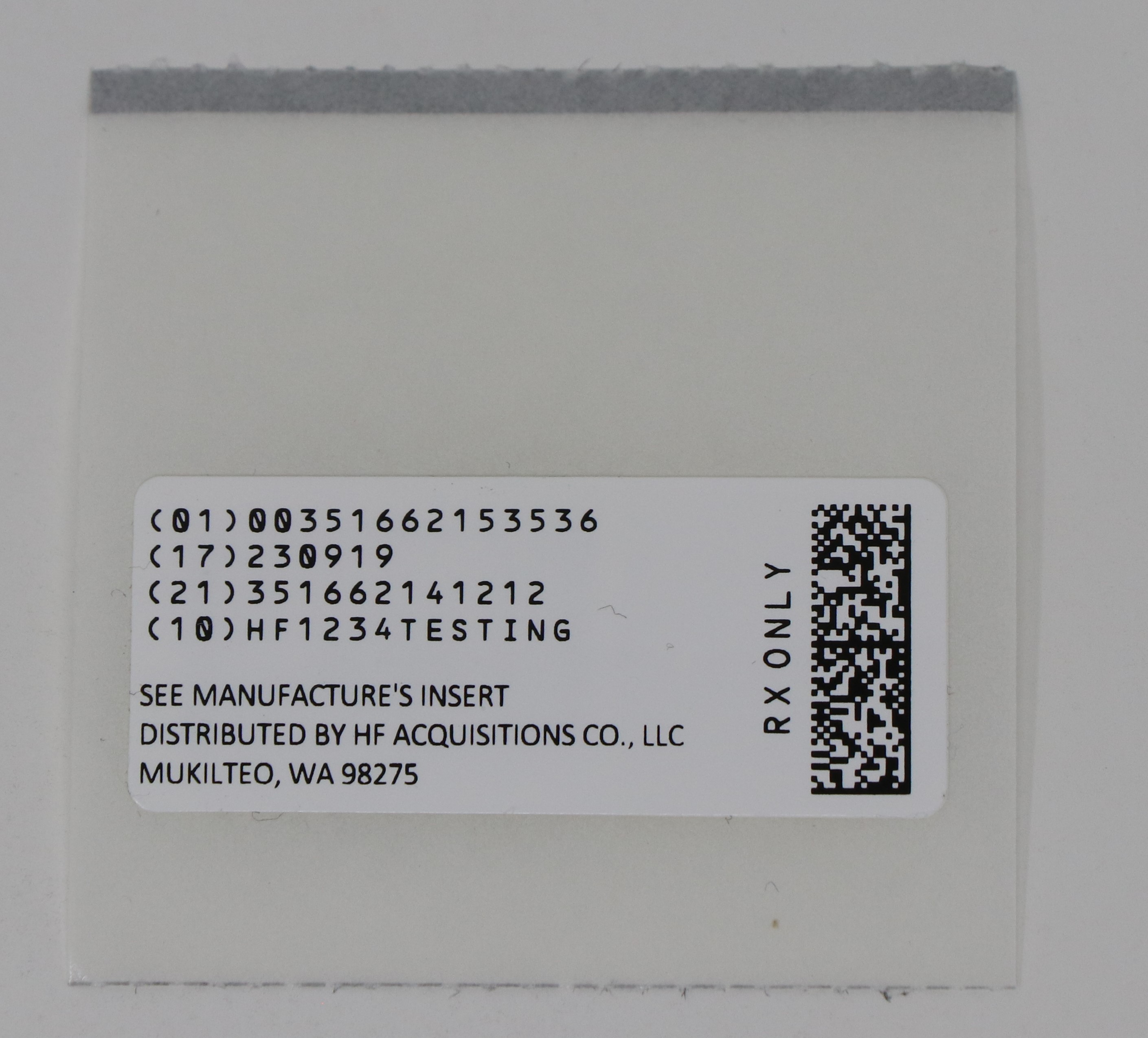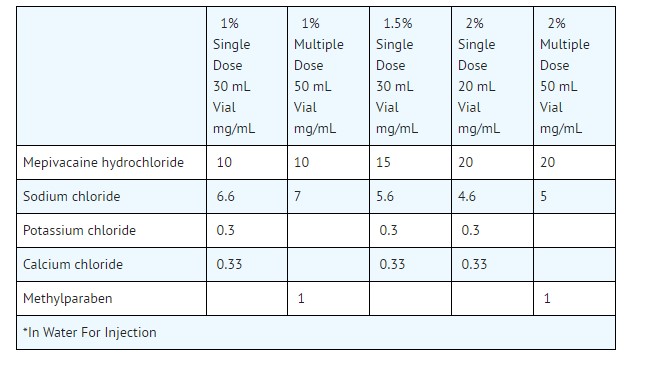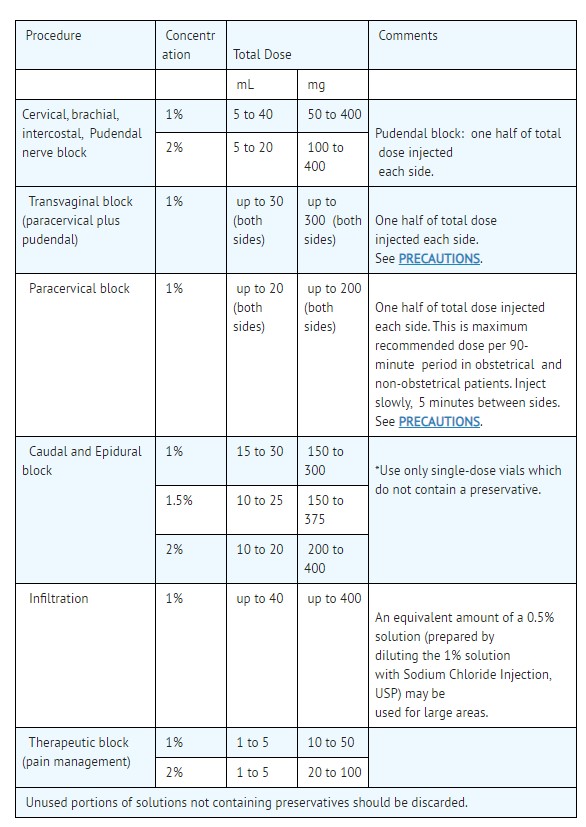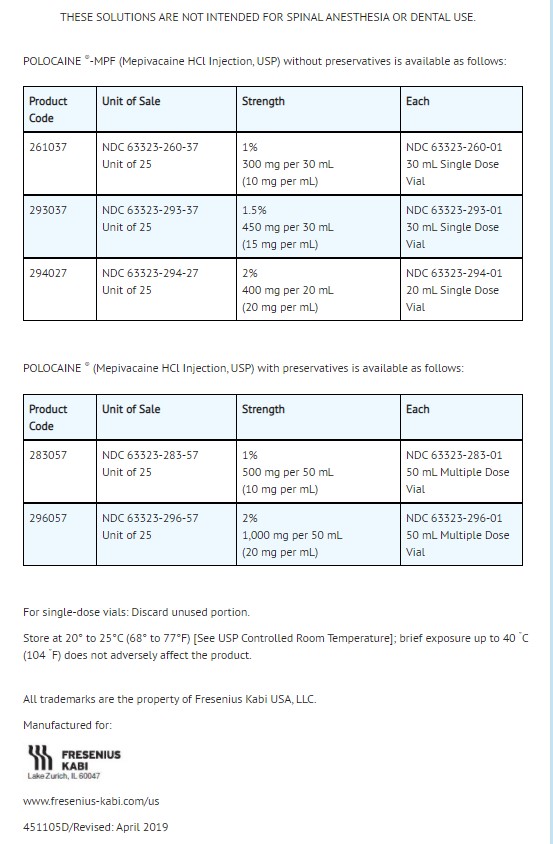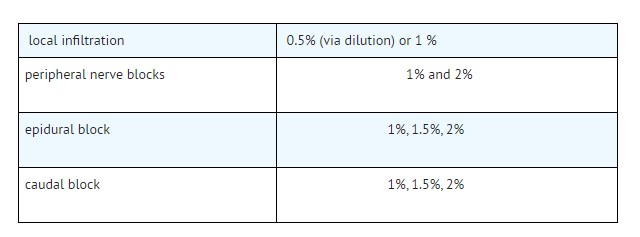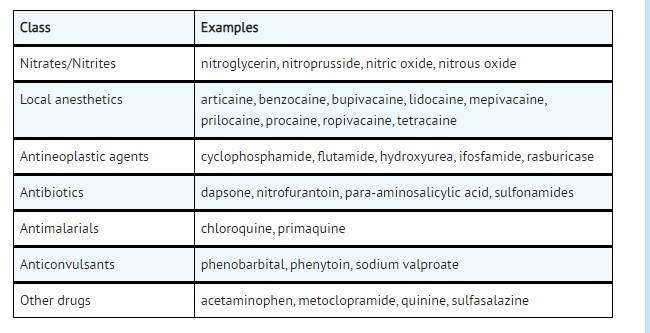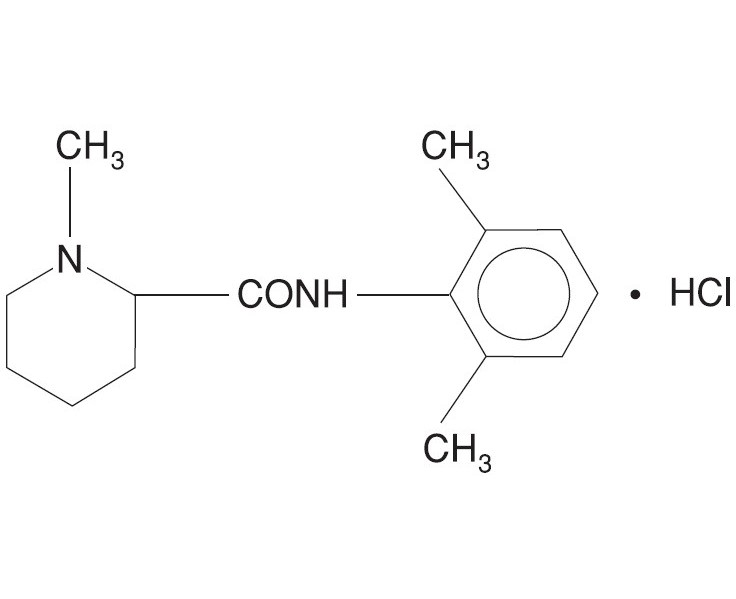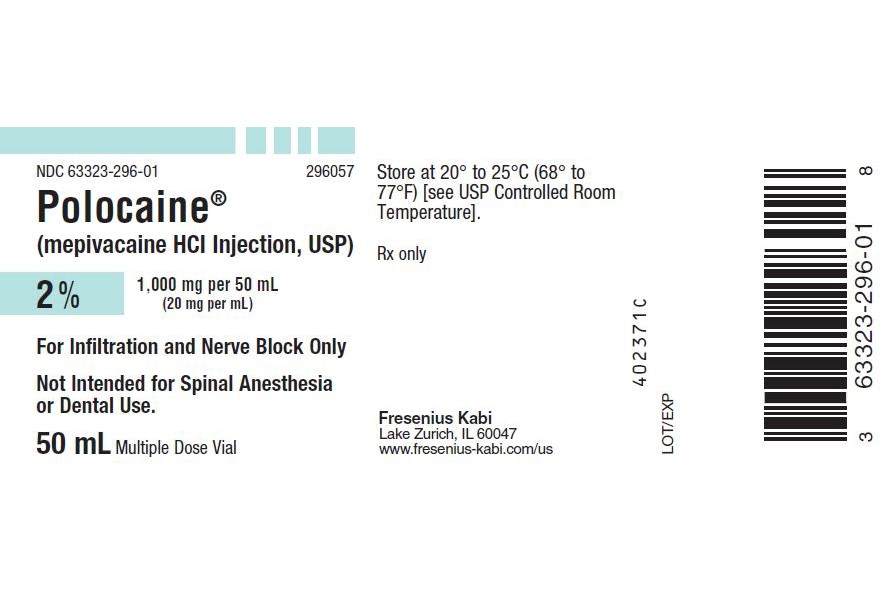 DRUG LABEL: POLOCAINE (MEPIVACAINE HCl)
NDC: 51662-1535 | Form: INJECTION, SOLUTION
Manufacturer: HF Acquisition Co LLC, DBA HealthFirst
Category: prescription | Type: HUMAN PRESCRIPTION DRUG LABEL
Date: 20240130

ACTIVE INGREDIENTS: MEPIVACAINE HYDROCHLORIDE 20 mg/1 mL
INACTIVE INGREDIENTS: METHYLPARABEN 1 mg/1 mL; SODIUM CHLORIDE 5 mg/1 mL; SODIUM HYDROXIDE; HYDROCHLORIC ACID

POLOCAINE (MEPIVACAINE HCl INJECTION, USP) 2% 1000mg/50mL (20mg/mL)

SPL UNCLASSIFIED

THESE SOLUTIONS ARE NOT INTENDED FOR SPINAL ANESTHESIA OR DENTAL USE

Rx only

DESCRIPTION

Mepivacaine hydrochloride is 2-Piperidinecarboxamide, N-(2, 6-dimethylphenyl)-1-methyl-, monohydrochloride and has the following structural formula:

C 15H 22N 2O • HCl

It is a white, crystalline, odorless powder, soluble in water, but very resistant to both acid and alkaline hydrolysis.

Mepivacaine hydrochloride is a local anesthetic available as sterile isotonic solutions (clear, colorless) in concentrations of 1%, 1.5% and 2% for injection via local infiltration, peripheral nerve block, and caudal and lumbar epidural blocks.

Mepivacaine hydrochloride is related chemically and pharmacologically to the amide-type local anesthetics. It contains an amide linkage between the aromatic nucleus and the amino group.
Composition of Available Solutions*

The pH of the solution is adjusted between 4.5 and 6.8 with sodium hydroxide or hydrochloric acid.

CLINICAL PHARMACOLOGY

Local anesthetics block the generation and the conduction of nerve impulses, presumably by increasing the threshold for electrical excitation in the nerve, by slowing the propagation of the nerve impulse, and by reducing the rate of rise of the action potential. In general, the progression of anesthesia is related to the diameter, myelination, and conduction velocity of affected nerve fibers. Clinically, the order of loss of nerve function is as follows: pain, temperature, touch, proprioception, and skeletal muscle tone.

Systemic absorption of local anesthetics produces effects on the cardiovascular and central nervous systems. At blood concentrations achieved with normal therapeutic doses, changes in cardiac conduction, excitability, refractoriness, contractility, and peripheral vascular resistance are minimal. However, toxic blood concentrations depress cardiac conduction and excitability, which may lead to atrioventricular block and ultimately to cardiac arrest. In addition, myocardial contractility is depressed and peripheral vasodilation occurs, leading to decreased cardiac output and arterial blood pressure.

Following systemic absorption, local anesthetics can produce central nervous system stimulation, depression, or both. Apparent central stimulation is manifested as restlessness, tremors, and shivering, progressing to convulsions, followed by depression and coma progressing ultimately to respiratory arrest. However, the local anesthetics have a primary depressant effect on the medulla and on higher centers. The depressed stage may occur without a prior excited stage.

A clinical study using 15 mL of 2% epidural mepivacaine at the T 9-10 interspace in 62 patients, 20 to 79 years of age, demonstrated a 40% decrease in the amount of mepivacaine required to block a given number of dermatomes in the elderly (60 to 79 years, N=13) as compared to young adults 20 to 39 years.

Another study using 10 mL of 2% lumbar epidural mepivacaine in 161 patients, 19 to 75 years of age, demonstrated a strong inverse relationship between patient age and the number of dermatomes blocked per cc of mepivacaine injected.

Pharmacokinetics

The rate of systemic absorption of local anesthetics is dependent upon the total dose and concentration of drug administered, the route of administration, the vascularity of the administration site, and the presence or absence of epinephrine in the anesthetic solution. A dilute concentration of epinephrine (1:200,000 or 5 mcg/mL) usually reduces the rate of absorption and plasma concentration of mepivacaine, however, it has been reported that vasoconstrictors do not significantly prolong anesthesia with mepivacaine.

Onset of anesthesia with mepivacaine is rapid, the time of onset for sensory block ranging from about 3 to 20 minutes depending upon such factors as the anesthetic technique, the type of block, the concentration of the solution, and the individual patient. The degree of motor blockade produced is dependent on the concentration of the solution. A 0.5% solution will be effective in small superficial nerve blocks while the 1% concentration will block sensory and sympathetic conduction without loss of motor function. The 1.5% solution will provide extensive and often complete motor block and the 2% concentration of mepivacaine hydrochloride will produce complete sensory and motor block of any nerve group.

The duration of anesthesia also varies depending upon the technique and type of block, the concentration, and the individual. Mepivacaine will normally provide anesthesia which is adequate for 2 to 2½ hours of surgery.

Local anesthetics are bound to plasma proteins in varying degrees. Generally, the lower the plasma concentration of drug, the higher the percentage of drug bound to plasma.
Local anesthetics appear to cross the placenta by passive diffusion. The rate and degree of diffusion is governed by the degree of plasma protein binding, the degree of ionization, and the degree of lipid solubility. Fetal/maternal ratios of local anesthetics appear to be inversely related to the degree of plasma protein binding, because only the free, unbound drug is available for placental transfer. Mepivacaine is approximately 75% bound to plasma proteins. The extent of placental transfer is also determined by the degree of ionization and lipid solubility of the drug. Lipid soluble, nonionized drugs readily enter the fetal blood from the maternal circulation.

Depending upon the route of administration, local anesthetics are distributed to some extent to all body tissues, with high concentrations found in highly perfused organs such as the liver, lungs, heart, and brain.

Various pharmacokinetic parameters of the local anesthetics can be significantly altered by the presence of hepatic or renal disease, addition of epinephrine, factors affecting urinary pH, renal blood flow, the route of drug administration, and the age of the patient. The half-life of mepivacaine in adults is 1.9 to 3.2 hours and in neonates 8.7 to 9 hours.

Mepivacaine, because of its amide structure, is not detoxified by the circulating plasma esterases. It is rapidly metabolized, with only a small percentage of the anesthetic (5 percent to 10 percent) being excreted unchanged in the urine. The liver is the principal site of metabolism, with over 50% of the administered dose being excreted into the bile as metabolites. Most of the metabolized mepivacaine is probably resorbed in the intestine and then excreted into the urine since only a small percentage is found in the feces. The principal route of excretion is via the kidney. Most of the anesthetic and its metabolites are eliminated within 30 hours. It has been shown that hydroxylation and N-demethylation, which are detoxification reactions, play important roles in the metabolism of the anesthetic. Three metabolites of mepivacaine have been identified from human adults: two phenols, which are excreted almost exclusively as their glucuronide conjugates, and the N-demethylated compound (2’, 6’-pipecoloxylidide).

INDICATIONS & USAGE

POLOCAINE (Mepivacaine HCl Injection, USP), is indicated for production of local or regional analgesia and anesthesia by local infiltration, peripheral nerve block techniques, and central neural techniques including epidural and caudal blocks.

The routes of administration and indicated concentrations for mepivacaine are:

See DOSAGE AND ADMINISTRATION for additional information. Standard textbooks should be consulted to determine the accepted procedures and techniques for the administration of mepivacaine.

CONTRAINDICATIONS

Mepivacaine is contraindicated in patients with a known hypersensitivity to it or to any local anesthetic agent of the amide-type or to other components of solutions of mepivacaine.

WARNINGS

LOCAL ANESTHETICS SHOULD ONLY BE EMPLOYED BY CLINICIANS WHO ARE WELL VERSED IN DIAGNOSIS AND MANAGEMENT OF DOSE-RELATED TOXICITY AND OTHER ACUTE EMERGENCIES WHICH MIGHT ARISE FROM THE BLOCK TO BE EMPLOYED, AND THEN ONLY AFTER INSURING THE IMMEDIATE AVAILABILITY OF OXYGEN, OTHER RESUSCITATIVE DRUGS, CARDIOPULMONARY RESUSCITATIVE EQUIPMENT, AND THE PERSONNEL RESOURCES NEEDED FOR PROPER MANAGEMENT OF TOXIC REACTIONS AND RELATED EMERGENCIES (see also ADVERSE REACTIONS and PRECAUTIONS). DELAY IN PROPER MANAGEMENT OF DOSE-RELATED TOXICITY, UNDERVENTILATION FROM ANY CAUSE, AND/OR ALTERED SENSITIVITY MAY LEAD TO THE DEVELOPMENT OF ACIDOSIS, CARDIAC ARREST AND, POSSIBLY, DEATH.

Methemoglobinemia

Cases of methemoglobinemia have been reported in association with local anesthetic use. Although all patients are at risk for methemoglobinemia, patients with glucose-6-phosphate dehydrogenase deficiency, congenital or idiopathic methemoglobinemia, cardiac or pulmonary compromise, infants under 6 months of age, and concurrent exposure to oxidizing agents or their metabolites are more susceptible to developing clinical manifestations of the condition. If local anesthetics must be used in these patients, close monitoring for symptoms and signs of methemoglobinemia is recommended.

Signs of methemoglobinemia may occur immediately or may be delayed some hours after exposure, and are characterized by a cyanotic skin discoloration and/or abnormal coloration of the blood. Methemoglobin levels may continue to rise; therefore, immediate treatment is required to avert more serious CNS and cardiovascular adverse effects, including seizures, coma, arrhythmias, and death. Discontinue Polocaine and any other oxidizing agents. Depending on the severity of the signs and symptoms, patients may respond to supportive care, i.e., oxygen therapy, hydration. A more severe clinical presentation may require treatment with methylene blue, exchange transfusion, or hyperbaric oxygen.

Local anesthetic solutions containing antimicrobial preservatives (ie, those supplied in multiple-dose vials) should not be used for epidural or caudal anesthesia because safety has not been established with regard to intrathecal injection, either intentionally or inadvertently, of such preservatives.

Intra-articular infusions of local anesthetics following arthroscopic and other surgical procedures is an unapproved use, and there have been post-marketing reports of chondrolysis in patients receiving such infusions. The majority of reported cases of chondrolysis have involved the shoulder joint; cases of gleno-humeral chondrolysis have been described in pediatric and adult patients following intra-articular infusions of local anesthetics with and without epinephrine for periods of 48 to 72 hours. There is insufficient information to determine whether shorter infusion periods are not associated with these findings. The time of onset of symptoms, such as joint pain, stiffness and loss of motion can be variable, but may begin as early as the 2nd month after surgery. Currently, there is no effective treatment for chondrolysis; patients who experienced chondrolysis have required additional diagnostic and therapeutic procedures and some required arthroplasty or shoulder replacement.

It is essential that aspiration for blood or cerebrospinal fluid (where applicable) be done prior to injecting any local anesthetic, both the original dose and all subsequent doses, to avoid intravascular or subarachnoid injection. However, a negative aspiration does not ensure against an intravascular or subarachnoid injection.

Reactions resulting in fatality have occurred on rare occasions with the use of local anesthetics.

Mepivacaine with epinephrine or other vasopressors should not be used concomitantly with ergot-type oxytocic drugs, because a severe persistent hypertension may occur. Likewise, solutions of mepivacaine containing a vasoconstrictor, such as epinephrine, should be used with extreme caution in patients receiving monoamine oxidase inhibitors (MAOI) or antidepressants of the triptyline or imipramine types, because severe prolonged hypertension may result.

Local anesthetic procedures should be used with caution when there is inflammation and/or sepsis in the region of the proposed injection.

Mixing or the prior or intercurrent use of any local anesthetic with mepivacaine cannot be recommended because of insufficient data on the clinical use of such mixtures.

PRECAUTIONS

General

The safety and effectiveness of local anesthetics depend on proper dosage, correct technique, adequate precautions, and readiness for emergencies. Resuscitative equipment, oxygen, and other resuscitative drugs should be available for immediate use (see WARNINGS and ADVERSE REACTIONS). During major regional nerve blocks, the patient should have IV fluids running via an indwelling catheter to assure a functioning intravenous pathway. The lowest dosage of local anesthetic that results in effective anesthesia should be used to avoid high plasma levels and serious adverse effects. Injections should be made slowly, with frequent aspirations before and during the injection to avoid intravascular injection. Current opinion favors fractional administration with constant attention to the patient, rather than rapid bolus injection. Syringe aspirations should also be performed before and during each supplemental injection in continuous (intermittent) catheter techniques. An intravascular injection is still possible even if aspirations for blood are negative.

During the administration of epidural anesthesia, it is recommended that a test dose be administered initially and the effects monitored before the full dose is given. When using a “continuous” catheter technique, test doses should be given prior to both the original and all reinforcing doses, because plastic tubing in the epidural space can migrate into a blood vessel or through the dura. When the clinical conditions permit, an effective test dose should contain epinephrine (10 mcg to 15 mcg have been suggested) to serve as a warning of unintended intravascular injection. If injected into a blood vessel, this amount of epinephrine is likely to produce an “epinephrine response” within 45 seconds, consisting of an increase of pulse and blood pressure, circumoral pallor, palpitations, and nervousness in the unsedated patient. The sedated patient may exhibit only a pulse rate increase of 20 or more beats per minute for 15 or more seconds. Therefore, following the test dose, the heart rate should be monitored for a heart rate increase. The test dose should also contain 45 mg to 50 mg of mepivacaine hydrochloride to detect an unintended intrathecal administration. This will be evidenced within a few minutes by signs of spinal block (eg, decreased sensation of the buttocks, paresis of the legs, or, in the sedated patient, absent knee jerk).

Injection of repeated doses of local anesthetics may cause significant increases in plasma levels with each repeated dose due to slow accumulation of the drug or its metabolites or to slow metabolic degradation. Tolerance to elevated blood levels varies with the status of the patient. Debilitated, elderly patients, and acutely ill patients should be given reduced doses commensurate with their age and physical status. Local anesthetics should also be used with caution in patients with severe disturbances of cardiac rhythm, shock, heart block, or hypotension.
Careful and constant monitoring of cardiovascular and respiratory (adequacy of ventilation) vital signs, and the patient’s state of consciousness should be performed after each local anesthetic injection. It should be kept in mind at such times that restlessness, anxiety, incoherent speech, lightheadedness, numbness and tingling of the mouth and lips, metallic taste, tinnitus, dizziness, blurred vision, tremors, twitching, depression, or drowsiness may be early warning signs of central nervous system toxicity.

Local anesthetic solutions containing a vasoconstrictor should be used cautiously and in carefully restricted quantities in areas of the body supplied by end arteries or having otherwise compromised blood supply such as digits, nose, external ear, penis. Patients with hypertensive vascular disease may exhibit exaggerated vasoconstrictor response. Ischemic injury or necrosis may result.

Mepivacaine should be used with caution in patients with known allergies and sensitivities.

Because amide-type local anesthetics such as mepivacaine are metabolized by the liver and excreted by the kidneys, these drugs, especially repeat doses, should be used cautiously in patients with hepatic and renal disease. Patients with severe hepatic disease, because of their inability to metabolize local anesthetics normally, are at greater risk of developing toxic plasma concentrations. Local anesthetics should also be used with caution in patients with impaired cardiovascular function because they may be less able to compensate for functional changes associated with the prolongation of AV conduction produced by these drugs.

Serious dose-related cardiac arrhythmias may occur if preparations containing a vasoconstrictor such as epinephrine are employed in patients during or following the administration of potent inhalation anesthetics. In deciding whether to use these products concurrently in the same patient, the combined action of both agents upon the myocardium, the concentration and volume of vasoconstrictor used, and the time since injection, when applicable, should be taken into account.

Many drugs used during the conduct of anesthesia are considered potential triggering agents for familial malignant hyperthermia. Because it is not known whether amide-type local anesthetics may trigger this reaction and because the need for supplemental general anesthesia cannot be predicted in advance, it is suggested that a standard protocol for management should be available. Early unexplained signs of tachycardia, tachypnea, labile blood pressure, and metabolic acidosis may precede temperature elevation. Successful outcome is dependent on early diagnosis, prompt discontinuance of the suspect triggering agent(s), and institution of treatment, including oxygen therapy, indicated supportive measures, and dantrolene. (Consult dantrolene sodium intravenous package insert before using.)

Use in Head and Neck Area

Small doses of local anesthetics injected into the head and neck area may produce adverse reactions similar to systemic toxicity seen with unintentional intravascular injections of larger doses. The injection procedures require the utmost care.

Confusion, convulsions, respiratory depression, and/or respiratory arrest, and cardiovascular stimulation or depression have been reported. These reactions may be due to intra-arterial injection of the local anesthetic with retrograde flow to the cerebral circulation. Patients receiving these blocks should have their circulation and respiration monitored and be constantly observed. Resuscitative equipment and personnel for treating adverse reactions should be immediately available. Dosage recommendations should not be exceeded.

Information for Patients

When appropriate, patients should be informed in advance that they may experience temporary loss of sensation and motor activity, usually in the lower half of the body, following proper administration of caudal or epidural anesthesia. Also, when appropriate, the physician should discuss other information including adverse reactions listed in this package insert.

Inform patients that use of local anesthetics may cause methemoglobinemia, a serious condition that must be treated promptly. Advise patients or caregivers to seek immediate medical attention if they or someone in their care experience the following signs or symptoms: pale, gray, or blue colored skin (cyanosis); headache; rapid heart rate; shortness of breath; lightheadedness; or fatigue.

Clinically Significant Drug Interactions

The administration of local anesthetic solutions containing epinephrine or norepinephrine to patients receiving monoamine oxidase inhibitors or tricyclic antidepressants may produce severe, prolonged hypertension. Concurrent use of these agents should generally be avoided. In situations when concurrent therapy is necessary, careful patient monitoring is essential.

Concurrent administration of vasopressor drugs and of ergot-type oxytocic drugs may cause severe, persistent hypertension or cerebrovascular accidents.

Phenothiazines and butyrophenones may reduce or reverse the pressor effect of epinephrine.

Patients who are administered local anesthetics are at increased risk of developing methemoglobinemia when concurrently exposed to the following drugs, which could include other local anesthetics:

Examples of Drugs Associated with Methemoglobinemia:

Carcinogenesis, Mutagenesis, Impairment of Fertility

Long-term studies in animals of most local anesthetics including mepivacaine to evaluate the carcinogenic potential have not been conducted. Mutagenic potential or the effect on fertility have not been determined. There is no evidence from human data that mepivacaine may be carcinogenic or mutagenic or that it impairs fertility.

Pregnancy

Animal reproduction studies have not been conducted with mepivacaine. There are no adequate and well-controlled studies in pregnant women of the effect of mepivacaine on the developing fetus. Mepivacaine hydrochloride should be used during pregnancy only if the potential benefit justifies the potential risk to the fetus. This does not preclude the use of mepivacaine at term for obstetrical anesthesia or analgesia (see LABOR AND DELIVERY).

Mepivacaine has been used for obstetrical analgesia by the epidural, caudal, and paracervical routes without evidence of adverse effects on the fetus when no more than the maximum safe dosages are used and strict adherence to technique is followed.

Labor and Delivery

Local anesthetics rapidly cross the placenta, and when used for epidural, paracervical, caudal, or pudendal block anesthesia, can cause varying degrees of maternal, fetal, and neonatal toxicity (see CLINICAL PHARMACOLOGY, PHARMACOKINETICS). The incidence and degree of toxicity depend upon the procedure performed, the type and amount of drug used, and the technique of drug administration. Adverse reactions in the parturient, fetus, and neonate involve alterations of the central nervous system, peripheral vascular tone, and cardiac function.

Maternal hypotension has resulted from regional anesthesia. Local anesthetics produce vasodilation by blocking sympathetic nerves. Elevating the patient’s legs and positioning her on her left side will help prevent decreases in blood pressure. The fetal heart rate also should be monitored continuously and electronic fetal monitoring is highly advisable.

Epidural, paracervical, caudal, or pudendal anesthesia may alter the forces of parturition through changes in uterine contractility or maternal expulsive efforts. In one study, paracervical block anesthesia was associated with a decrease in the mean duration of first stage labor and facilitation of cervical dilation. Epidural anesthesia has been reported to prolong the second stage of labor by removing the parturient’s reflex urge to bear down or by interfering with motor function. The use of obstetrical anesthesia may increase the need for forceps assistance.

The use of some local anesthetic drug products during labor and delivery may be followed by diminished muscle strength and tone for the first day or two of life. The long-term significance of these observations is unknown.

Fetal bradycardia may occur in 20 to 30 percent of patients receiving para-cervical block anesthesia with the amide-type local anesthetics and may be associated with fetal acidosis. Fetal heart rate should always be monitored during paracervical anesthesia. Added risk appears to be present in prematurity, postmaturity, toxemia of pregnancy, and fetal distress. The physician should weigh the possible advantages against dangers when considering paracervical block in these conditions. Careful adherence to recommended dosage is of the utmost importance in obstetrical paracervical block. Failure to achieve adequate analgesia with recommended doses should arouse suspicion of intravascular or fetal intracranial injection.

Cases compatible with unintended fetal intracranial injection of local anesthetic solution have been reported following intended paracervical or pudendal block or both. Babies so affected present with unexplained neonatal depression at birth which correlates with high local anesthetic serum levels and usually manifest seizures within six hours. Prompt use of supportive measures combined with forced urinary excretion of the local anesthetic has been used successfully to manage this complication.

Case reports of maternal convulsions and cardiovascular collapse following use of some local anesthetics for paracervical block in early pregnancy (as anesthesia for elective abortion) suggest that systemic absorption under these circumstances may be rapid. The recommended maximum dose of the local anesthetic should not be exceeded. Injection should be made slowly and with frequent aspiration. Allow a five-minute interval between sides.

It is extremely important to avoid aortocaval compression by the gravid uterus during administration of regional block to parturients. To do this, the patient must be maintained in the left lateral decubitus position or a blanket roll or sandbag may be placed beneath the right hip and the gravid uterus displaced to the left.

Nursing Mothers

It is not known whether local anesthetic drugs are excreted in human milk. Because many drugs are excreted in human milk, caution should be exercised when local anesthetics are administered to a nursing woman.

Pediatric Use

Guidelines for the administration of mepivacaine to pediatric patients are presented in DOSAGE AND ADMINISTRATION.

Geriatric Use

Clinical studies and other reported clinical experience indicates that use of the drug in elderly patients requires a decreased dosage (see CLINICAL PHARMACOLOGY, PRECAUTIONS, GENERAL, and DOSAGE AND ADMINISTRATION).

Mepivacaine and mepivacaine metabolites are known to be substantially excreted by the kidney, and the risk of toxic reactions to this drug may be greater in patients with impaired renal function. Because elderly patients are more likely to have decreased renal function, care should be taken in dose selection, and it may be useful to monitor renal function.

ADVERSE REACTIONS

To report SUSPECTED ADVERSE REACTIONS, contact Fresenius Kabi USA, LLC at 1-800-551-7176 or FDA at 1-800-FDA-1088 or www.fda.gov/medwatch.

Reactions to mepivacaine are characteristic of those associated with other amide-type local anesthetics. A major cause of adverse reactions to this group of drugs is excessive plasma levels, which may be due to overdosage, inadvertent intravascular injection, or slow metabolic degradation.

Systemic

The most commonly encountered acute adverse experiences which demand immediate countermeasures are related to the central nervous system and the cardiovascular system. These adverse experiences are generally dose related and due to high plasma levels which may result from overdosage, rapid absorption from the injection site, diminished tolerance, or from unintentional intravascular injection of the local anesthetic solution. In addition to systemic dose-related toxicity, unintentional subarachnoid injection of drug during the intended performance of caudal or lumbar epidural block or nerve blocks near the vertebral column (especially in the head and neck region) may result in underventilation or apnea (“Total or High Spinal”). Also, hypotension due to loss of sympathetic tone and respiratory paralysis or underventilation due to cephalad extension of the motor level of anesthesia may occur. This may lead to secondary cardiac arrest if untreated. Factors influencing plasma protein binding, such as acidosis, systemic diseases which alter protein production, or competition of other drugs for protein binding sites, may diminish individual tolerance.

Central Nervous System Reactions

These are characterized by excitation and/or depression. Restlessness, anxiety, dizziness, tinnitus, blurred vision, or tremors may occur, possibly proceeding to convulsions. However, excitement may be transient or absent, with depression being the first manifestation of an adverse reaction. This may quickly be followed by drowsiness merging into unconsciousness and respiratory arrest. Other central nervous system effects may be nausea, vomiting, chills, and constriction of the pupils.

The incidence of convulsions associated with the use of local anesthetics varies with the procedure used and the total dose administered. In a survey of studies of epidural anesthesia, overt toxicity progressing to convulsions occurred in approximately 0.1% of local anesthetic administrations.

Cardiovascular Reactions

High doses or, inadvertent intravascular injection, may lead to high plasma levels and related depression of the myocardium, decreased cardiac output, heart block, hypotension (or sometimes hypertension), bradycardia, ventricular arrhythmias, and possibly cardiac arrest (see WARNINGS, PRECAUTIONS, and OVERDOSAGE).

Allergic

Allergic-type reactions are rare and may occur as a result of sensitivity to the local anesthetic or to other formulation ingredients, such as the antimicrobial preservative methylparaben, contained in multiple-dose vials. These reactions are characterized by signs such as urticaria, pruritus, erythema, angioneurotic edema (including laryngeal edema), tachycardia, sneezing, nausea, vomiting, dizziness, syncope, excessive sweating, elevated temperature, and possibly, anaphylactoid-like symptomatology (including severe hypotension). Cross sensitivity among members of the amide-type local anesthetic group has been reported. The usefulness of screening for sensitivity has not been definitely established.

Neurologic

The incidences of adverse neurologic reactions associated with the use of local anesthetics may be related to the total dose of local anesthetic administered and are also dependent upon the particular drug used, the route of administration, and the physical status of the patient. Many of these effects may be related to local anesthetic techniques, with or without a contribution from the drug.

In the practice of caudal or lumbar epidural block, occasional unintentional penetration of the subarachnoid space by the catheter or needle may occur. Subsequent adverse effects may depend partially on the amount of drug administered intrathecally and the physiological and physical effects of a dural puncture. A high spinal is characterized by paralysis of the legs, loss of consciousness, respiratory paralysis, and bradycardia.

Neurologic effects following epidural or caudal anesthesia may include spinal block of varying magnitude (including high or total spinal block); hypotension secondary to spinal block; urinary retention; fecal and urinary incontinence; loss of perineal sensation and sexual function; persistent anesthesia, paresthesia, weakness, paralysis of the lower extremities, and loss of sphincter control all of which may have slow, incomplete, or no recovery; headache; backache; septic meningitis; meningismus; slowing of labor; increased incidence of forceps delivery; cranial nerve palsies due to traction on nerves from loss of cerebrospinal fluid.

Neurologic effects following other procedures or routes of administration may include persistent anesthesia, paresthesia, weakness, paralysis, all of which may have slow, incomplete or no recovery.

OVERDOSAGE

Acute emergencies from local anesthetics are generally related to high plasma levels encountered during therapeutic use of local anesthetics or to unintended subarachnoid injection of local anesthetic solution (see ADVERSE REACTIONS, WARNINGS, and PRECAUTIONS).

Management of Local Anesthetic Emergencies

The first consideration is prevention, best accomplished by careful and constant monitoring of cardiovascular and respiratory vital signs and the patient’s state of consciousness after each local anesthetic injection. At the first sign of change, oxygen should be administered.
The first step in the management of systemic toxic reactions, as well as underventilation or apnea due to unintentional subarachnoid injection of drug solution, consists of immediate attention to the establishment and maintenance of a patent airway and effective assisted or controlled ventilation with 100% oxygen with a delivery system capable of permitting immediate positive airway pressure by mask. This may prevent convulsions if they have not already occurred.

If necessary, use drugs to control the convulsions. A 50 mg to 100 mg bolus IV injection of succinylcholine will paralyze the patient without depressing the central nervous or cardiovascular systems and facilitate ventilation. A bolus IV dose of 5 mg to 10 mg of diazepam or 50 mg to 100 mg of thiopental will permit ventilation and counteract central nervous system stimulation, but these drugs also depress central nervous system, respiratory, and cardiac function, add to postictal depression and may result in apnea. Intravenous barbiturates, anticonvulsant agents, or muscle relaxants should only be administered by those familiar with their use. Immediately after the institution of these ventilatory measures, the adequacy of the circulation should be evaluated. Supportive treatment of circulatory depression may require administration of intravenous fluids, and when appropriate, a vasopressor dictated by the clinical situation (such as ephedrine or epinephrine to enhance myocardial contractile force).

Endotracheal intubation, employing drugs and techniques familiar to the clinician may be indicated after initial administration of oxygen by mask, if difficulty is encountered in the maintenance of patent airway or if prolonged ventilatory support (assisted or controlled) is indicated.

Recent clinical data from patients experiencing local anesthetic induced convulsions demonstrated rapid development of hypoxia, hypercarbia, and acidosis within a minute of the onset of convulsions. These observations suggest that oxygen consumption and carbon dioxide production are greatly increased during local anesthetic convulsions and emphasize the importance of immediate and effective ventilation with oxygen which may avoid cardiac arrest.

If not treated immediately, convulsions with simultaneous hypoxia, hypercarbia, and acidosis, plus myocardial depression from the direct effects of the local anesthetic may result in cardiac arrhythmias, bradycardia, asystole, ventricular fibrillation, or cardiac arrest. Respiratory abnormalities, including apnea, may occur. Underventilation or apnea due to unintentional subarachnoid injection of local anesthetic solution may produce these same signs and also lead to cardiac arrest if ventilatory support is not instituted. If cardiac arrest should occur, standard cardiopulmonary resuscitative measures should be instituted and maintained for a prolonged period if necessary. Recovery has been reported after prolonged resuscitative efforts.

The supine position is dangerous in pregnant women at term because of aortocaval compression by the gravid uterus. Therefore, during treatment of systemic toxicity, maternal hypotension, or fetal bradycardia following regional block, the parturient should be maintained in the left lateral decubitus position if possible, or manual displacement of the uterus off the great vessels should be accomplished.

The mean seizure dosage of mepivacaine in rhesus monkeys was found to be 18.8 mg/kg with mean arterial plasma concentration of 24.4 mcg/mL. The intravenous and subcutaneous LD 50 in mice is 23 mg/kg to 35 mg/kg and 280 mg/kg respectively.

DOSAGE & ADMINISTRATION

The dose of any local anesthetic administered varies with the anesthetic procedure, the area to be anesthetized, the vascularity of the tissues, the number of neuronal segments to be blocked, the depth of anesthesia and degree of muscle relaxation required, the duration of anesthesia desired, individual tolerance and the physical condition of the patient. The smallest dose and concentration required to produce the desired result should be administered. Dosages of mepivacaine hydrochloride should be reduced for elderly and debilitated patients and patients with cardiac and/or liver disease. The rapid injection of a large volume of local anesthetic solution should be avoided and fractional doses should be used when feasible.

For specific techniques and procedures, refer to standard textbooks.
There have been adverse event reports of chondrolysis in patients receiving intra-articular infusions of local anesthetics following arthroscopic and other surgical procedures. Polocaine is not approved for this use (see WARNINGS and DOSAGE AND ADMINISTRATION).

The recommended single adult dose (or the total of a series of doses given in one procedure) of mepivacaine hydrochloride for unsedated, healthy, normal-sized individuals should not usually exceed 400 mg. The recommended dosage is based on requirements for the average adult and should be reduced for elderly or debilitated patients.

While maximum doses of 7 mg/kg (550 mg) have been administered without adverse effect, these are not recommended, except in exceptional circumstances and under no circumstances should the administration be repeated at intervals of less than 1½ hours. The total dose for any 24-hour period should not exceed 1,000 mg because of a slow accumulation of the anesthetic or its derivatives or slower than normal metabolic degradation or detoxification with repeat administration (see CLINICAL PHARMACOLOGY and PRECAUTIONS).

Pediatric patients tolerate the local anesthetic as well as adults. However, the pediatric dose should be carefully measured as a percentage of the total adult dose based on weight, and should not exceed 5 mg/kg to 6 mg/kg (2.5 mg/lb to 3 mg/lb) in pediatric patients, especially those weighing less than 30 lbs. In pediatric patients under 3 years of age or weighing less than 30 lbs concentrations less than 2% (eg, 0.5% to 1.5%) should be employed.

Unused portions of solutions not containing preservatives, ie, those supplied in single-dose vials, should be discarded following initial use.

This product should be inspected visually for particulate matter and discoloration prior to administration whenever solution and container permit. Solutions which are discolored or which contain particulate matter should not be administered.
Recommended Concentrations and Doses of Mepivacaine Hydrochloride

* Dosage forms listed as POLOCAINE-MPF (Mepivacaine HCl Injection, USP) are single-dose solutions which do not contain a preservative.

HOW SUPPLIED

POLOCAINE (MEPIVACAINE HCl INJECTION, USP) is supplied in the following dosage forms.

NDC 51662-1535-2 POLOCAINE (MEPIVACAINE HCl INJECTION, USP) 2% 1000mg/50mL (20mg/mL) 50mL VIAL

NDC 51662-1535-3 POLOCAINE (MEPIVACAINE HCl INJECTION, USP) 2% 1000mg/50mL (20mg/mL) 50mL VIAL (25/BX)

HF Acquisition Co LLC, DBA HealthFirst Mukilteo, WA 98275

Also supplied in the following manufacture supplied dosage forms:

PRINCIPAL DISPLAY PANEL - 51662-1535 - POLOCAINE (MEPIVACAINE HCl INJECTION, USP) 2% 1000mg/50mL (20mg/mL)

VIAL LABEL

51662-1535-2, POUCH LABELING

51662-1535-3, SERIALIZED LABELING

51662-1535-3, BOX LABELING